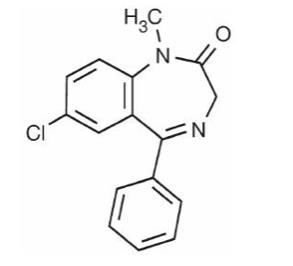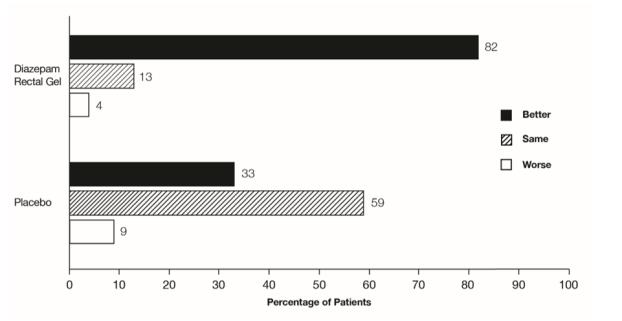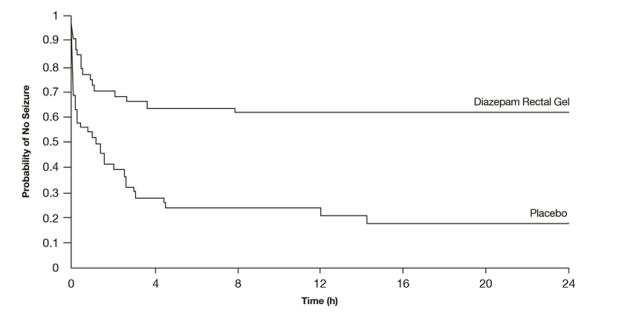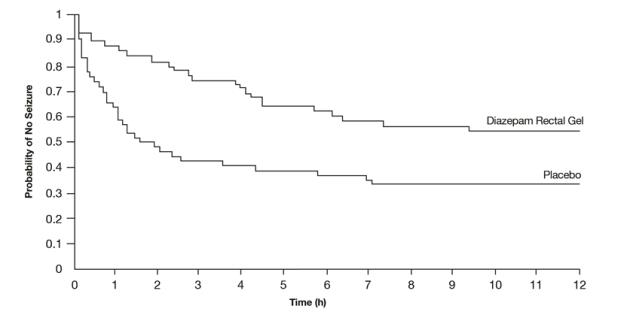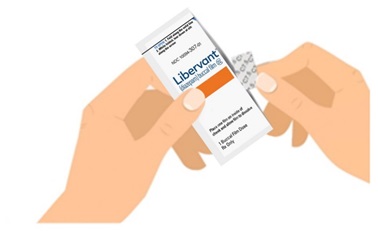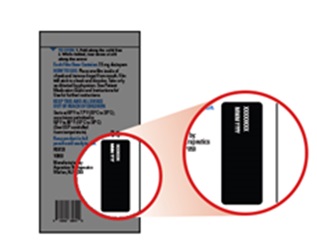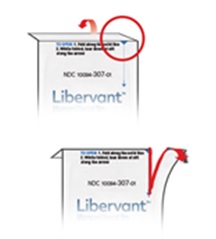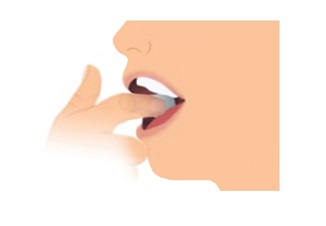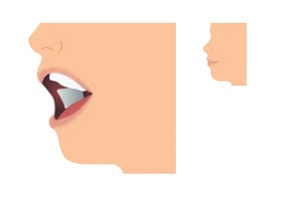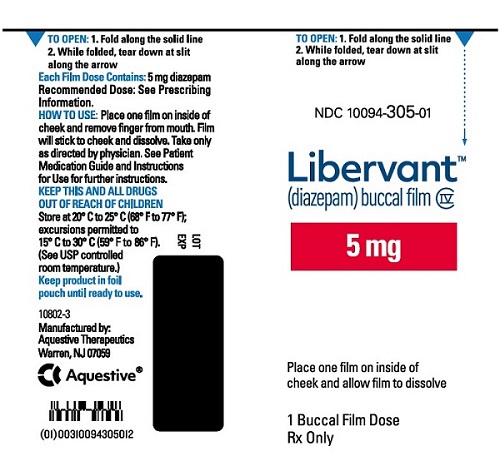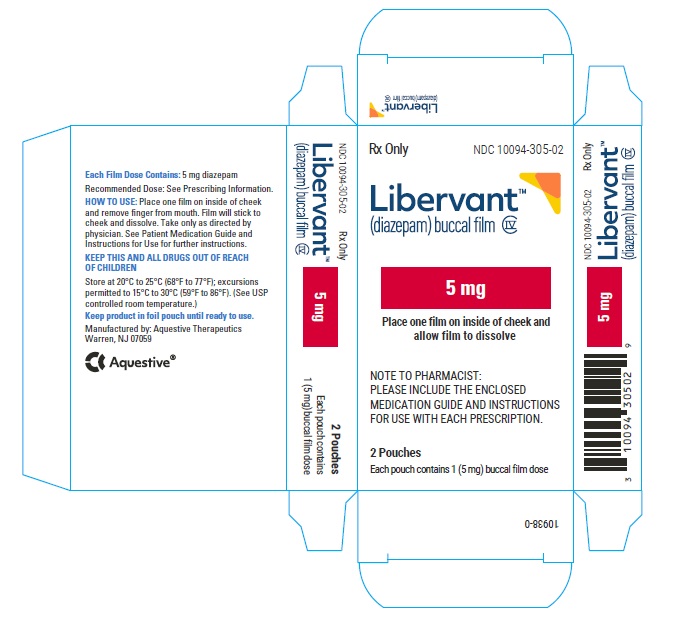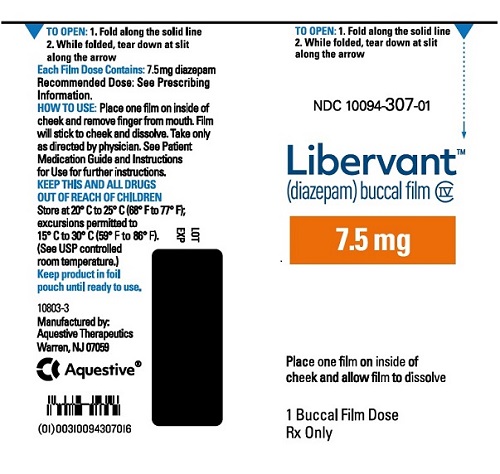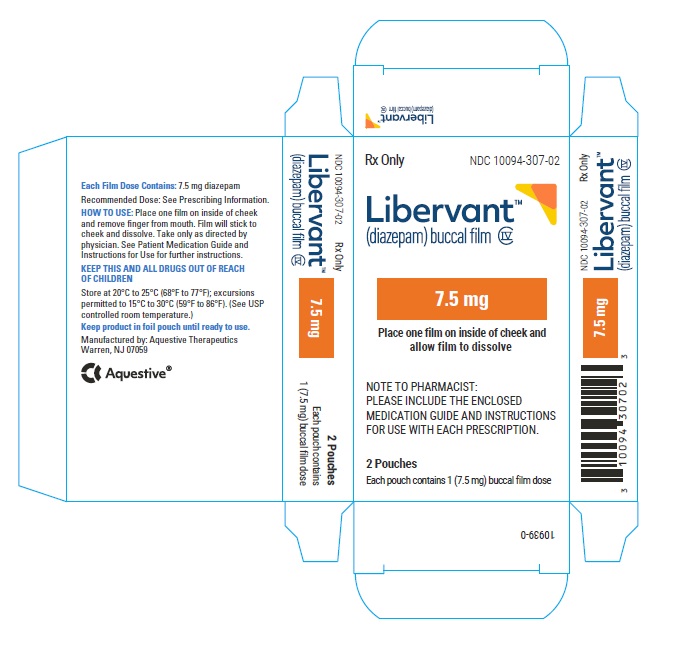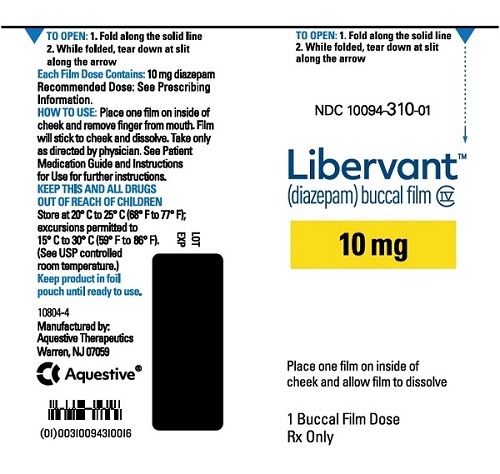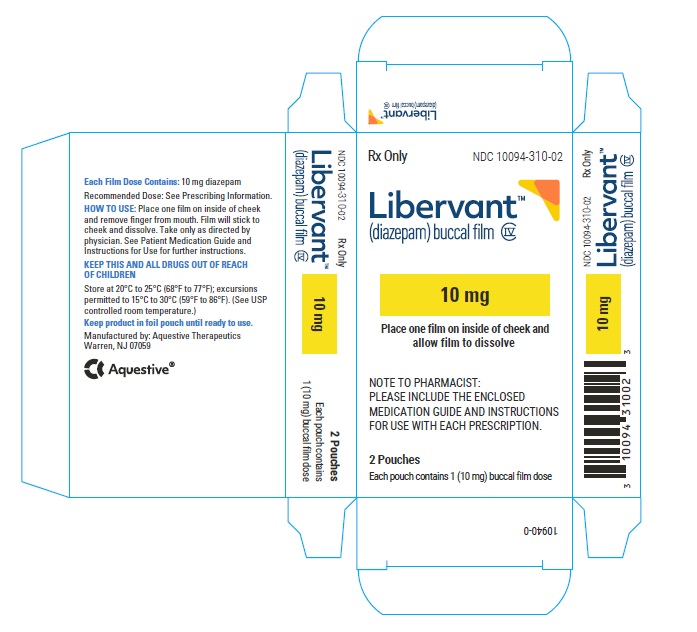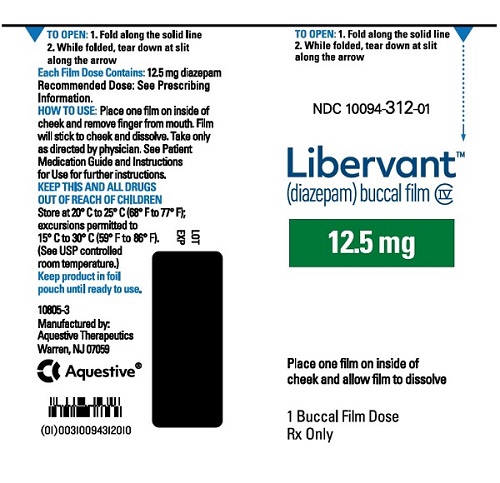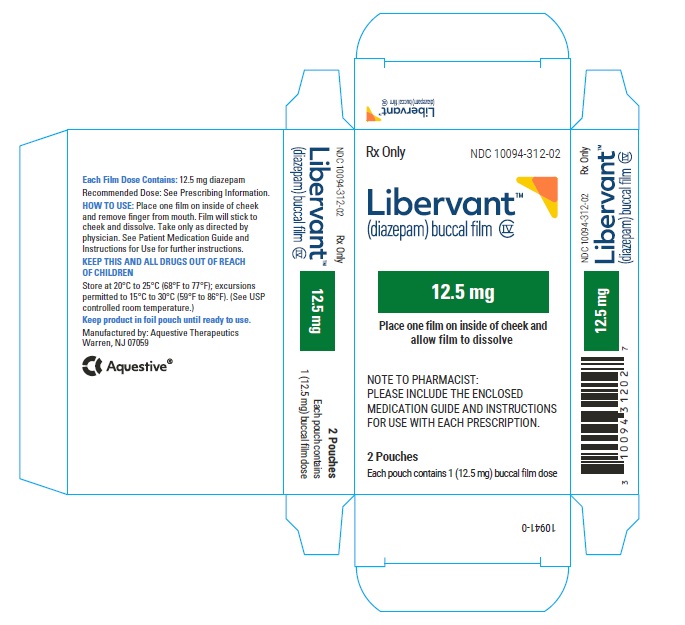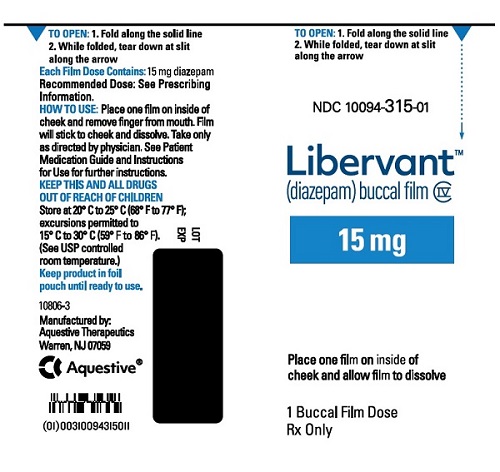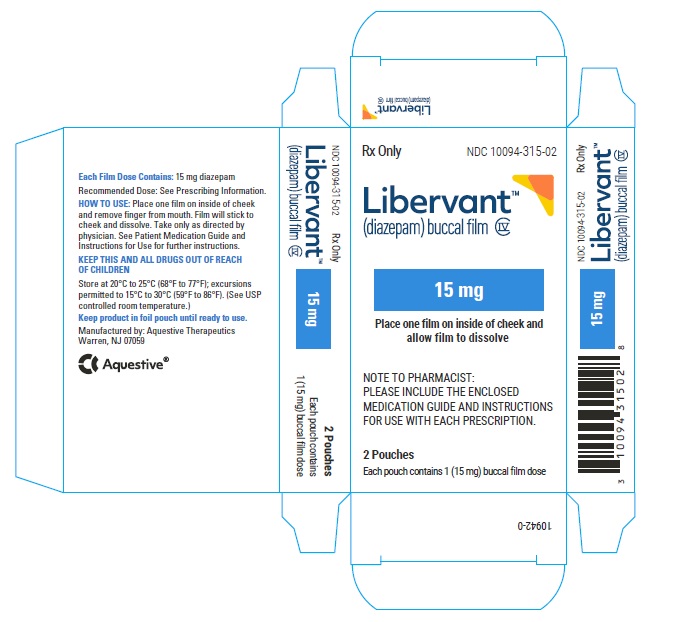 DRUG LABEL: LIBERVANT
NDC: 10094-305 | Form: FILM
Manufacturer: AQUESTIVE THERAPEUTICS
Category: prescription | Type: HUMAN PRESCRIPTION DRUG LABEL
Date: 20241113
DEA Schedule: CIV

ACTIVE INGREDIENTS: DIAZEPAM 5 mg/1 1
INACTIVE INGREDIENTS: BENZYL ALCOHOL; CLOVE OIL; FD&C GREEN NO. 3; GLYCERYL MONOOLEATE; HYPROMELLOSES; PEPPERMINT OIL; POLYETHYLENE GLYCOL, UNSPECIFIED; SODIUM PHOSPHATE; SUCRALOSE; VANILLIN; XANTHAN GUM; WATER; POVIDONE K90; EDETATE DISODIUM

HIGHLIGHTS OF PRESCRIBING INFORMATION

These highlights do not include all the information needed to use LIBERVANTTM safely and effectively. See full prescribing information for LIBERVANT.
LIBERVANT (diazepam) buccal film, C-IV
Initial U.S. Approval: 1963

WARNING: RISKS FROM CONCOMITANT USE WITH OPIOIDS; ABUSE, MISUSE, AND ADDICTION and DEPENDENCE AND WITHDRAWAL REACTIONS

See full prescribing information for complete boxed warning.

- Concomitant use of benzodiazepines and opioids may result in profound sedation, respiratory depression, coma, and death. (5.1, 7.1)
- LIBERVANT is approved for use in pediatric patients 2 to 5 years of age. The unapproved use of LIBERVANT exposes users to risks of abuse, misuse, and addiction, which can lead to overdose or death. Before prescribing LIBERVANT and throughout treatment, assess each patient’s risk for abuse, misuse, and addiction. (5.2)
- Although LIBERVANT is indicated only for intermittent use (1, 2), if used more frequently than recommended, abrupt discontinuation or rapid dosage reduction of LIBERVANT may precipitate acute withdrawal reactions, which can be life-threatening. For patients using LIBERVANT more frequently than recommended, to reduce the risk of withdrawal reactions, use a gradual taper to discontinue LIBERVANT. (5.3)

1 INDICATIONS AND USAGE

LIBERVANT is a benzodiazepine indicated for the acute treatment of intermittent, stereotypic episodes of frequent seizure activity (i.e., seizure clusters, acute repetitive seizures) that are distinct from a patient’s usual seizure pattern in patients with epilepsy 2 to 5 years of age. (1)

2 DOSAGE AND ADMINISTRATION

The recommended dose of LIBERVANT is dependent on the patient’s weight. See dosing table for specific recommendations. (2.2)

3 DOSAGE FORMS AND STRENGTHS

Buccal film: 5 mg, 7.5 mg, 10 mg, 12.5 mg, 15 mg (3)

4 CONTRAINDICATIONS

- Hypersensitivity to diazepam (4)
- Acute-narrow angle glaucoma (4, 5.4)

5 WARNINGS AND PRECAUTIONS

- CNS Depression: Monitor for central nervous system (CNS) depression. Risk may be increased with concomitant use of alcohol or other CNS depressants. (5.2,5.4, 7.2)
- Suicidal Behavior and Ideation: Antiepileptic drugs increase the risk of suicidal thoughts and behavior. (5.5)
- Glaucoma: Can increase intraocular pressure; use in patients with open-angle glaucoma only if receiving appropriate therapy. (4, 5.6)

6 ADVERSE REACTIONS

- The most common adverse reactions (> 4%) were somnolence and headache. (6)

To report SUSPECTED ADVERSE REACTIONS, contact Aquestive Therapeutics, Inc. at 1-877-394-5045 or FDA at 1-800-FDA-1088 or www.fda.gov/medwatch.

7 DRUG INTERACTIONS

- CYP2C19 and CYP3A4 Inhibitors: Could decrease the rate of diazepam elimination; adverse reactions may be increased. (7.3)
- CYP2C19 and CYP3A4 Inducers: Exposure of diazepam after LIBERVANT administration may be decreased; efficacy may be decreased. (7.3)

FULL PRESCRIBING INFORMATION

WARNING: RISKS FROM CONCOMITANT USE WITH OPIOIDS; ABUSE, MISUSE, AND ADDICTION and DEPENDENCE AND WITHDRAWAL REACTIONS

- Concomitant use of benzodiazepines and opioids may result in profound sedation, respiratory depression, coma, and death. Reserve concomitant prescribing of these drugs for patients for whom alternative treatment options are inadequate. Limit dosages and durations to the minimum required. Follow patients for signs and symptoms of respiratory depression and sedation [see Warnings and Precautions (5.1), Drug Interactions (7.1)].
- LIBERVANT is approved for use in pediatric patients 2 to 5 years of age. The unapproved use of LIBERVANT exposes users to risks of abuse, misuse, and addiction, which can lead to overdose or death. Abuse and misuse of benzodiazepines commonly involve concomitant use of other medications, alcohol, and/or illicit substances, which is associated with an increased frequency of serious adverse outcomes [see Warnings and Precautions (5.2)].
- The continued use of benzodiazepines may lead to clinically significant physical dependence. The risks of dependence and withdrawal increase with longer treatment duration and higher daily dose. Although LIBERVANT is indicated only for intermittent use [see Indications and Usage (1) and Dosage and Administration (2)], if used more frequently than recommended, abrupt discontinuation or rapid dosage reduction of LIBERVANT may precipitate acute withdrawal reactions, which can be life-threatening. For patients using LIBERVANT more frequently than recommended, to reduce the risk of withdrawal reactions, use a gradual taper to discontinue LIBERVANT [see Warnings and Precautions (5.3)].

1 INDICATIONS AND USAGE

LIBERVANT is indicated for the acute treatment of intermittent, stereotypic episodes of frequent seizure activity (i.e., seizure clusters, acute repetitive seizures) that are distinct from a patient’s usual seizure pattern in patients with epilepsy 2 to 5 years of age.

2 DOSAGE AND ADMINISTRATION

2.1 Instructions Prior to Dosing

Prior to treatment, healthcare professionals should instruct the individual administering LIBERVANT on how to identify seizure clusters and use the product appropriately [see Dosage and Administration (2.3) and Patient Counseling Information (17)].

2.2 Dosage Information

The recommended dose of LIBERVANT is dependent on the patient’s weight and is provided in Table 1.

Table 1: Recommended Dosage for Pediatric Patients 2 to 5 Years of Age
Weight | Libervant Dose
6 kg to 10 kg | 5 mg
11 kg to 15 kg | 7.5 mg
16 kg to 20 kg | 10 mg
21 kg to 25 kg | 12.5 mg
26 kg to 30 kg | 15 mg

Second Dose (if needed): A second dose, when required, may be administered at least 4 hours after the first dose.

Maximum Dosage and Treatment Frequency: Do not use more than 2 doses of LIBERVANT to treat a single episode.

Do not use LIBERVANT to treat more than one episode every five days or more than five episodes per month.

2.3 Important Administration Instructions

Caregivers should be counseled to read carefully the “Instructions for Use” for complete directions on how to properly administer LIBERVANT.

LIBERVANT is a rectangular green buccal film that dissolves when applied on the inside of the mouth on top of the surface of the cheek. Do not split LIBERVANT, the entire dose should be applied and allowed to dissolve [see Dosage and Administration (2.1)]. Do not administer LIBERVANT buccal film with liquids.

LIBERVANT dosing may be administered without regard to food [see Clinical Pharmacology (12.3)].

3 DOSAGE FORMS AND STRENGTHS

LIBERVANT buccal film: green, rectangular, orally dissolving film strips:

- 5 mg film imprinted with D5
- 7.5 mg film imprinted with D7•5
- 10 mg film imprinted with D10
- 12.5 mg film imprinted with D12•5
- 15 mg film imprinted with D15

4 CONTRAINDICATIONS

LIBERVANT is contraindicated in patients with:

- Hypersensitivity to diazepam
- Acute narrow-angle glaucoma [see Warnings and Precautions (5.6)]

5 WARNINGS AND PRECAUTIONS

5.1 Risks from Concomitant Use with Opioids

Concomitant use of benzodiazepines, including LIBERVANT, and opioids may result in profound sedation, respiratory depression, coma, and death. Because of these risks, reserve concomitant prescribing of benzodiazepines and opioids for patients for whom alternative treatment options are inadequate.

Observational studies have demonstrated that concomitant use of opioid analgesics and benzodiazepines increases the risk of drug-related mortality compared to use of opioids alone. If a decision is made to prescribe LIBERVANT concomitantly with opioids, prescribe the lowest effective dosages and minimum durations of concomitant use, and follow patients closely for signs and symptoms of respiratory depression and sedation. Advise caregivers about the risks of respiratory depression and sedation when LIBERVANT is used with opioids [see Drug Interactions (7.1)].

5.2 Abuse, Misuse, and Addiction

LIBERVANT is approved for use in pediatric patients 2 to 5 years of age. The unapproved use of LIBERVANT exposes users to the risks of abuse, misuse, and addiction, which can lead to overdose or death. Abuse and misuse of benzodiazepines often (but not always) involve the use of doses greater than the maximum recommended dosage and commonly involve concomitant use of other medications, alcohol, and/or illicit substances, which is associated with an increased frequency of serious adverse outcomes, including respiratory depression, overdose, or death [see Drug Abuse and Dependence (9.2)].

5.3 Dependence and Withdrawal Reactions After Use of LIBERVANT More Frequently Than Recommended

For patients using LIBERVANT more frequently than recommended, to reduce the risk of withdrawal reactions, use a gradual taper to discontinue LIBERVANT (a patient-specific plan should be used to taper the dose).

Patients at an increased risk of withdrawal adverse reactions after benzodiazepine discontinuation or rapid dosage reduction include those who take higher dosages, and those who have had longer durations of use.

Acute Withdrawal Reactions

The continued use of benzodiazepines may lead to clinically significant physical dependence. Although LIBERVANT is indicated only for intermittent use [see Indications and Usage (1) and Dosage and Administration (2)], if used more frequently than recommended, abrupt discontinuation or rapid dosage reduction of LIBERVANT, or administration of flumazenil (a benzodiazepine antagonist) may precipitate acute withdrawal reactions, which can be life-threatening (e.g., seizures) [see Drug Abuse and Dependence (9.3)].

Protracted Withdrawal Syndrome

In some cases, benzodiazepine users have developed a protracted withdrawal syndrome with withdrawal symptoms lasting weeks to more than 12 months [see Drug Abuse and Dependence (9.3)].

5.4 Central Nervous System (CNS) Depression

Because LIBERVANT produces CNS depression, patients receiving this drug, who are otherwise capable and qualified to do so should be cautioned against engaging in hazardous occupations requiring mental alertness, such as operating machinery, driving a motor vehicle, or riding a bicycle, until the effects of the drug, such as drowsiness, have subsided, and as their medical condition permits.

Although LIBERVANT is indicated for use solely on an intermittent basis, the potential for a synergistic CNS-depressant effect when used simultaneously with alcohol or other CNS depressants must be considered by the prescriber, and appropriate recommendations made to the patient and/or caregiver.

5.5 Suicidal Behavior and Ideation

Antiepileptic drugs (AEDs), including LIBERVANT, increase the risk of suicidal thoughts or behavior in patients taking these drugs for any indication. Patients treated with any AED for any indication should be monitored for the emergence or worsening of depression, suicidal thoughts or behavior, and/or any unusual changes in mood or behavior.

Pooled analyses of 199 placebo-controlled clinical trials (mono- and adjunctive therapy) of 11 different AEDs showed that patients randomized to one of the AEDs had approximately twice the risk (adjusted Relative Risk 1.8, 95% CI:1.2, 2.7) of suicidal thinking or behavior compared to patients randomized to placebo. In these trials, which had a median treatment duration of 12 weeks, the estimated incidence rate of suicidal behavior or ideation among 27,863 AED-treated patients was 0.43%, compared to 0.24% among 16,029 placebo-treated patients, representing an increase of approximately one case of suicidal thinking or behavior for every 530 patients treated. There were four suicides in drug-treated patients in the trials and none in placebo-treated patients, but the number is too small to allow any conclusion about drug effect on suicide.

The increased risk of suicidal thoughts or behavior with AEDs was observed as early as one week after starting drug treatment with AEDs and persisted for the duration of treatment assessed. Because most trials included in the analysis did not extend beyond 24 weeks, the risk of suicidal thoughts or behavior beyond 24 weeks could not be assessed. The risk of suicidal thoughts or behavior was generally consistent among drugs in the data analyzed. The finding of increased risk with AEDs of varying mechanisms of action and across a range of indications suggests that the risk applies to all AEDs used for any indication. The risk did not vary substantially by age (5-100 years) in the clinical trials analyzed. Table 2 shows absolute and relative risk by indication for all evaluated AEDs.

Table 2: Risk by Indication for Antiepileptic Drugs in the Pooled Analysis
Indication | Placebo Patients with Events per 1000 Patients | Drug Patients with Events per 1000 Patients | Relative Risk: Incidence of Drug Events in Drug Patients / Incidence in Placebo Patients | Risk Difference: Additional Drug Patients with Events per 1000 Patients
Epilepsy | 1.0 | 3.4 | 3.5 | 2.4
Psychiatric | 5.7 | 8.5 | 1.5 | 2.9
Other | 1.0 | 1.8 | 1.9 | 0.9
Total | 2.4 | 4.3 | 1.8 | 1.9

The relative risk for suicidal thoughts or behavior was higher in clinical trials for epilepsy than in clinical trials for psychiatric or other conditions, but the absolute risk differences were similar for the epilepsy and psychiatric indications.

Anyone considering prescribing LIBERVANT, or any other AED, must balance the risk of suicidal thoughts or behaviors with the risk of untreated illness. Epilepsy and many other illnesses for which AEDs are prescribed are themselves associated with morbidity and mortality and an increased risk of suicidal thoughts and behavior. Should suicidal thoughts and behavior emerge during treatment, the prescriber needs to consider whether the emergence of these symptoms in any given patient may be related to the illness being treated.

5.6 Glaucoma

Benzodiazepines, including LIBERVANT, can increase intraocular pressure in patients with glaucoma. LIBERVANT may be used in patients with open-angle glaucoma only if they are receiving appropriate therapy. LIBERVANT is contraindicated in patients with narrow-angle glaucoma.

5.7 Neonatal Sedation and Withdrawal Syndrome

LIBERVANT is not approved for use in adolescents and adults. Unapproved use of LIBERVANT in adolescents and adults late in pregnancy can result in sedation (respiratory depression, lethargy, hypotonia) and/or withdrawal symptoms (hyperreflexia, irritability, restlessness, tremors, inconsolable crying, and feeding difficulties) in the neonate [see Use in Specific Populations (8.1)]. Monitor neonates exposed to LIBERVANT during pregnancy or labor for signs of sedation and monitor neonates exposed to LIBERVANT during pregnancy for signs of withdrawal; manage these neonates accordingly.

5.8 Risk of Serious Adverse Reactions in Infants due to Benzyl Alcohol Preservative

LIBERVANT is not approved for use in neonates or infants. Serious and fatal adverse reactions including “gasping syndrome” can occur in neonates and low birth weight infants treated with benzyl alcohol-preserved drugs, including LIBERVANT. The “gasping syndrome” is characterized by central nervous system depression, metabolic acidosis, and gasping respirations. The minimum amount of benzyl alcohol at which serious adverse reactions may occur is not known (LIBERVANT contains 3.96 to 11.87 mg of benzyl alcohol per buccal film) [see Use in Specific Populations (8.4)].

6 ADVERSE REACTIONS

The following serious adverse reactions are described elsewhere in the labeling.

- Risk of Concomitant Use with Opioids [see Warnings and Precautions (5.1)]
- Abuse, Misuse, and Addiction [see Warnings and Precautions (5.2)]
- Dependence and Withdrawal Reactions After Use of LIBERVANT More Frequently Than Recommended [see Warnings and Precautions (5.3)]
- CNS depression [see Warnings and Precautions (5.4)]
- Suicidal Behavior and Ideation [see Warnings and Precautions (5.5)]
- Glaucoma [see Warnings and Precautions (5.6)]
- Neonatal Sedation and Withdrawal Syndrome [see Warnings and Precautions (5.7)]
- Risk of Serious Adverse Reactions in Infants due to Benzyl Alcohol Preservative [see Warnings and Precautions (5.8)]

6.1 Clinical Trials Experience

Because clinical trials are conducted under widely varying conditions, adverse reaction rates observed in the clinical trials of a drug cannot be directly compared to rates in the clinical trials of another drug and may not reflect the rates observed in practice. The safety of LIBERVANT is supported by clinical trials using diazepam rectal gel; pharmacokinetic studies of LIBERVANT in healthy subjects and epilepsy patients; and an open-label long-term safety and tolerability study of LIBERVANT in epilepsy patients.

Diazepam Rectal Gel

In studies previously conducted with diazepam rectal gel, adverse event data were collected from double-blind, placebo-controlled studies and open-label studies. The majority of adverse events were mild to moderate in severity and transient in nature.

Two patients who received diazepam rectal gel died seven to 15 weeks following treatment; neither of these deaths was deemed related to diazepam rectal gel.

The most frequent adverse reactions (at least 5%) in the two double-blind, placebo-controlled studies were somnolence and headache. Table 3 lists adverse reactions that occurred in greater than 1% of patients enrolled in parallel-group, placebo-controlled trials and were numerically more common in the diazepam rectal gel group than placebo. Adverse reactions were usually mild or moderate in intensity.

Approximately 1.4% of the 573 patients who received diazepam rectal gel in clinical trials of epilepsy discontinued treatment because of an adverse event. The adverse reaction most frequently associated with discontinuation (occurring in three patients) was somnolence. Other adverse reactions most commonly associated with discontinuation and occurring in two patients were hypoventilation and rash. Adverse reactions associated with discontinuation occurring in one patient were asthenia, hyperkinesia, incoordination, vasodilatation, and urticaria.

In the two double-blind, placebo-controlled, parallel-group studies [see Clinical Studies (14)], the proportion of patients who discontinued treatment because of adverse events was 2% for the group treated with diazepam rectal gel, versus 2% for the placebo group. In the diazepam rectal gel group, one patient discontinued because of rash and one patient discontinued because of lethargy.

Table 3: Adverse Reactions That Occurred in Greater Than 1% Of Patients in Parallel-Group, Placebo-Controlled Trials with Diazepam Rectal Gel and Were More Common Than in the Placebo Group
Adverse Reaction | Diazepam Rectal Gel N = 101 % | Placebo N = 104 %
Somnolence | 23 | 8
Headache | 5 | 4
Diarrhea | 4 | <1
Ataxia | 3 | <1
Dizziness | 3 | 2
Euphoria | 3 | 0
Incoordination | 3 | 0
Rash | 3 | 0
Asthma | 2 | 0
Vasodilatation | 2 | 0

LIBERVANT (Diazepam Buccal Film)

Clinical studies, which included patients with epilepsy 2 to 5 years of age, were conducted to support the safety and tolerability of LIBERVANT for the treatment of acute repetitive seizures. A total of 197 patients received LIBERVANT, of whom 107 received LIBERVANT for at least 6 months, and 48 for at least 1 year. The adverse reactions reported in these studies were similar to those seen in efficacy trials of diazepam rectal gel.

Other Adverse Reactions

Diazepam rectal gel was administered to 573 patients with epilepsy during all clinical trials, only some of which were placebo controlled. All of the events listed below occurred in at least 1% of the 573 individuals exposed to diazepam rectal gel.

Body as a Whole: Asthenia

Cardiovascular: Hypotension, vasodilatation

Nervous: Agitation, confusion, convulsion, dysarthria, emotional lability, speech disorder, thinking abnormal, vertigo

Respiratory: Hiccup

The following infrequent adverse events have been reported previously with diazepam use: depression, slurred speech, syncope, constipation, changes in libido, urinary retention, bradycardia, cardiovascular collapse, nystagmus, urticaria, neutropenia, and jaundice.

Paradoxical reactions such as acute hyperexcited states, anxiety, hallucinations, increased muscle spasticity, insomnia, rage, sleep disturbances and stimulation have been reported with other diazepam products. If these events occur with the use of LIBERVANT, the prescriber should consider discontinuation of use.

7 DRUG INTERACTIONS

7.1 Effect of Concomitant Use of Benzodiazepines and Opioids

The concomitant use of benzodiazepines and opioids increases the risk of respiratory depression because of actions at different receptor sites in the CNS that control respiration. Benzodiazepines interact at GABAA sites, and opioids interact primarily at mu receptors. When benzodiazepines and opioids are combined, the potential for benzodiazepines to significantly worsen opioid-related respiratory depression exists. Limit dosage and duration of concomitant use of benzodiazepines and opioids and follow patients closely for respiratory depression and sedation [see Warnings and Precautions (5.1)].

7.2 CNS Depressants and Alcohol

Coadministration of other CNS depressants (e.g., valproate) or consumption of alcohol may potentiate the CNS-depressant effects of diazepam [see Warnings and Precautions (5.2)].

7.3 Effect of Other Drugs on LIBERVANT Metabolism

Potential interactions may occur when diazepam is given concurrently with agents that affect CYP2C19 and CYP3A4 activity.

Inhibitors of CYP2C19 and CYP3A4

Inhibitors of CYP2C19 (e.g., cimetidine, quinidine, and tranylcypromine) and CYP3A4 (e.g., ketoconazole, troleandomycin, and clotrimazole) could decrease the rate of diazepam elimination; therefore, adverse reactions to LIBERVANT may be increased.

Inducers of CYP2C19 and CYP3A4

Inducers of CYP2C19 (e.g., rifampin) and CYP3A4 (e.g., carbamazepine, phenytoin, dexamethasone, and phenobarbital) could increase the rate of diazepam elimination; therefore, efficacy of LIBERVANT may be decreased.

7.4 Effect of LIBERVANT on the Metabolism of Other Drugs

Diazepam is a substrate for CYP2C19 and CYP3A4; therefore, it is possible that LIBERVANT may interfere with the metabolism of drugs which are substrates for CYP2C19, (e.g. omeprazole, propranolol, and imipramine) and CYP3A4 (e.g. cyclosporine, paclitaxel, theophylline, and warfarin) leading to a potential drug-drug interaction [see Clinical Pharmacology (12.3)].

8 USE IN SPECIFIC POPULATIONS

8.1 Pregnancy

LIBERVANT is indicated for treatment in patients 2 to 5 years of age [see Indications and Usage (1)]. LIBERVANT is not approved for use in adolescents and adults.

Pregnancy Exposure Registry

There is a pregnancy exposure registry that monitors pregnancy outcomes in women exposed to antiepileptic drugs (AEDs), such as LIBERVANT, during pregnancy. Healthcare providers are encouraged to recommend that pregnant women who are taking LIBERVANT during pregnancy enroll in the North American Antiepileptic Drug (NAAED) Pregnancy Registry by calling 1-888-233-2334 or visiting http://www.aedpregnancyregistry.org/.

Risk Summary

Neonates born to mothers using benzodiazepines late in pregnancy have been reported to experience symptoms of sedation and/or neonatal withdrawal [see Warnings and Precautions (5.7) and Clinical Considerations]. Available data from published observational studies of pregnant women exposed to benzodiazepines do not report a clear association with benzodiazepines and major birth defects (see Human Data).

In animal studies, administration of diazepam during the organogenesis period of pregnancy resulted in increased incidences of fetal malformations at doses greater than those used clinically. Data for diazepam and other benzodiazepines suggest the possibility of increased neuronal cell death and long-term effects on neurobehavioral and immunological function based on findings in animals following prenatal or early postnatal exposure at clinically relevant doses (see Animal Data).

The background risk of major birth defects and miscarriage for the indicated population is unknown. All pregnancies have a background risk of birth defect, loss, or other adverse outcomes. In the U.S. general population, the estimated background risk of major birth defects and miscarriage in clinically recognized pregnancies is 2% to 4% and 15% to 20%, respectively.

Clinical Considerations

Fetal/Neonatal Adverse Reactions

Benzodiazepines cross the placenta and may produce respiratory depression, hypotonia, and sedation in neonates. Monitor neonates exposed to LIBERVANT during pregnancy or labor for signs of sedation, respiratory depression, hypotonia, and feeding problems. Monitor neonates exposed to LIBERVANT during pregnancy for signs of withdrawal. Manage these neonates accordingly [see Warnings and Precautions (5.7)].

Data

Human Data

Published data from observational studies on the use of benzodiazepines during pregnancy do not report a clear association with benzodiazepines and major birth defects.

Although early studies reported an increased risk of congenital malformations with diazepam and chlordiazepoxide, there was no consistent pattern noted. In addition, the majority of more recent case-control and cohort studies of benzodiazepine use during pregnancy, which were adjusted for confounding exposures to alcohol, tobacco and other medications, have not confirmed these findings.

Animal Data

Diazepam has been shown to produce increased incidences of fetal malformations in mice and hamsters when given orally at single doses of 100 mg/kg or greater (approximately 13 times a human dose of 0.6 mg/kg/day or greater on a mg/m^2 basis). Cleft palate and exencephaly are the most common and consistently reported malformations produced in these species by administration of high, maternally toxic doses of diazepam during organogenesis.

In published animal studies, administration of benzodiazepines or other drugs that enhance GABAergic neurotransmission to neonatal rats has been reported to result in widespread apoptotic neurodegeneration in the developing brain at plasma concentrations relevant for seizure control in humans. The window of vulnerability to these changes in rats (postnatal days 0-14) includes a period of brain development corresponding to that taking place during the third trimester of pregnancy in humans.

8.2 Lactation

LIBERVANT is indicated for treatment in patients 2 to 5 years of age [see Indications and Usage (1)]. LIBERVANT is not approved for use in adolescents and adults.

Risk Summary

Diazepam is excreted in human milk.

There are reports of sedation, poor feeding and poor weight gain in infants exposed to benzodiazepines through breast milk. There are no data to assess the effects of diazepam and/or its active metabolite(s) on milk production.

The developmental and health benefits of breastfeeding should be considered along with the mother's clinical need for LIBERVANT and any potential adverse effects on the breastfed infant from LIBERVANT or from the underlying maternal condition.

Clinical Considerations

Infants exposed to LIBERVANT through breast milk should be monitored for sedation, poor feeding, and poor weight gain.

8.4 Pediatric Use

Safety and effectiveness of LIBERVANT have been established in pediatric patients 2 to 5 years of age. Use of LIBERVANT in this age group is supported by evidence from adequate and well-controlled studies of diazepam rectal gel in adult and pediatric patients, adult bioavailability studies comparing LIBERVANT with diazepam rectal gel, pediatric and adult LIBERVANT pharmacokinetic data, and an open-label safety study of LIBERVANT including patients 2 years to 5 years of age [see Adverse Reactions (6.1), Clinical Pharmacology (12.3), and Clinical Studies (14)].

Safety and effectiveness of LIBERVANT in pediatric patients below the age of 2 and above the age of 5 have not been established.

LIBERVANT is not approved for use in neonates or infants.

- Prolonged CNS depression has been observed in neonates treated with diazepam.
- Serious adverse reactions including fatal reactions and the “gasping syndrome” occurred in premature neonates and low-birth-weight infants in the neonatal intensive care unit who received drugs containing benzyl alcohol as a preservative. In these cases, benzyl alcohol dosages of 99 to 234 mg/kg/day produced high levels of benzyl alcohol and its metabolites in the blood and urine (blood levels of benzyl alcohol were 0.61 to 1.378 mmol/L). Additional adverse reactions included gradual neurological deterioration, seizures, intracranial hemorrhage, hematologic abnormalities, skin breakdown, hepatic and renal failure, hypotension, bradycardia, and cardiovascular collapse. Preterm, low-birth-weight infants may be more likely to develop these reactions because they may be less able to metabolize benzyl alcohol. The minimum amount of benzyl alcohol at which serious adverse reactions may occur is not known (LIBERVANT contains 3.96 to 11.87 mg of benzyl alcohol per buccal film [see Warnings and Precautions (5.8)].

8.5 Geriatric Use

LIBERVANT is indicated for treatment in patients 2 to 5 years of age [see Indications and Usage (1)]. LIBERVANT is not approved for use in adults.

Clinical studies of LIBERVANT did not include sufficient numbers of subjects aged 65 and over to determine whether they respond differently from younger subjects.

A study of single dose IV administration of diazepam (0.1 mg/kg) indicates that the elimination half-life of diazepam increases linearly with age, ranging from about 15 hours at 18 years (healthy young adults) to about 100 hours at 95 years (healthy elderly) with a corresponding decrease in clearance of free diazepam.

If used in elderly patients, LIBERVANT should be used with caution because of an increase in half life with a corresponding decrease in the clearance of free diazepam [see Clinical Pharmacology (12.3)]. It is also recommended that the dosage be decreased to reduce the likelihood of ataxia or oversedation.

8.6 Compromised Respiratory Function

LIBERVANT should be used with caution in patients with compromised respiratory function related to a concurrent disease process (e.g., asthma, pneumonia) or neurologic damage.

9 DRUG ABUSE AND DEPENDENCE

9.1 Controlled Substance

LIBERVANT contains diazepam, a Schedule IV controlled substance.

9.2 Abuse

LIBERVANT is a benzodiazepine and a CNS depressant with a potential for abuse and addiction with unapproved use in adolescents and adults. Abuse is the intentional, non-therapeutic use of a drug, even once, for its desirable psychological or physiological effects. Misuse is the intentional use, for therapeutic purposes, of a drug by an individual in a way other than prescribed by a health care provider or for whom it was not prescribed. Drug addiction is a cluster of behavioral, cognitive, and physiological phenomena that may include a strong desire to take the drug, difficulties in controlling drug use (e.g., continuing drug use despite harmful consequences, giving a higher priority to drug use than other activities and obligations), and possible tolerance or physical dependence. Even taking benzodiazepines as prescribed may put patients at risk for abuse and misuse of their medication. Abuse and misuse of benzodiazepines may lead to addiction.

Abuse and misuse of benzodiazepines often (but not always) involve the use of doses greater than the maximum recommended dosage and commonly involve concomitant use of other medications, alcohol, and/or illicit substances, which is associated with an increased frequency of serious adverse outcomes, including respiratory depression, overdose, or death. Benzodiazepines are often sought by individuals who abuse drugs and other substances, and by individuals with addictive disorders [see Warnings and Precautions (5.2)].

The following adverse reactions have occurred with benzodiazepine abuse and/or misuse: abdominal pain, amnesia, anorexia, anxiety, aggression, ataxia, blurred vision, confusion, depression, disinhibition, disorientation, dizziness, euphoria, impaired concentration and memory, indigestion, irritability, muscle pain, slurred speech, tremors, and vertigo.

The following severe adverse reactions have occurred with benzodiazepine abuse and/or misuse: delirium, paranoia, suicidal ideation and behavior, seizures, coma, breathing difficulty, and death. Death is more often associated with polysubstance use (especially benzodiazepines with other CNS depressants such as opioids and alcohol).

9.3 Dependence

Physical Dependence After Use of LIBERVANT More Frequently Than Recommended

LIBERVANT may produce physical dependence if used more frequently than recommended. Physical dependence is a state that develops as a result of physiological adaptation in response to repeated drug use, manifested by withdrawal signs and symptoms after abrupt discontinuation or a significant dose reduction of a drug. Although LIBERVANT is indicated only for intermittent use [see Indications and Usage (1) and Dosage and Administration (2)], if used more frequently than recommended, abrupt discontinuation or rapid dosage reduction or administration of flumazenil, a benzodiazepine antagonist, may precipitate acute withdrawal reactions, including seizures, which can be life-threatening. Patients at an increased risk of withdrawal adverse reactions after benzodiazepine discontinuation or rapid dosage reduction include those who take higher dosages (i.e., higher and/or more frequent doses) and those who have had longer durations of use [see Warnings and Precautions (5.3)].

For patients using LIBERVANT more frequently than recommended, to reduce the risk of withdrawal reactions, use a gradual taper to discontinue LIBERVANT [see Warnings and Precautions (5.3)].

Acute Withdrawal Signs and Symptoms

Acute withdrawal signs and symptoms associated with benzodiazepines have included abnormal involuntary movements, anxiety, blurred vision, depersonalization, depression, derealization, dizziness, fatigue, gastrointestinal adverse reactions (e.g., nausea, vomiting, diarrhea, weight loss, decreased appetite), headache, hyperacusis, hypertension, irritability, insomnia, memory impairment, muscle pain and stiffness, panic attacks, photophobia, restlessness, tachycardia, and tremor. More severe acute withdrawal signs and symptoms, including life-threatening reactions, have included catatonia, convulsions, delirium tremens, depression, hallucinations, mania, psychosis, seizures, and suicidality.

Protracted Withdrawal Syndrome

Protracted withdrawal syndrome associated with benzodiazepines is characterized by anxiety, cognitive impairment, depression, insomnia, formication, motor symptoms (e.g., weakness, tremor, muscle twitches), paresthesia, and tinnitus that persists beyond 4 to 6 weeks after initial benzodiazepine withdrawal. Protracted withdrawal symptoms may last weeks to more than 12 months. As a result, there may be difficulty in differentiating withdrawal symptoms from potential re-emergence or continuation of symptoms for which the benzodiazepine was being used.

Tolerance

Tolerance to LIBERVANT may develop after use more frequently than recommended. Tolerance is a physiological state characterized by a reduced response to a drug after repeated administration (i.e., a higher dose of a drug is required to produce the same effect that was once obtained at a lower dose). Tolerance to the therapeutic effect of benzodiazepines may develop; however, little tolerance develops to the amnestic reactions and other cognitive impairments caused by benzodiazepines.

It is recommended that patients be treated with LIBERVANT no more frequently than one episode every five days and no more than five episodes per month.

LIBERVANT is not recommended for chronic, daily use as an anticonvulsant. Chronic daily use of diazepam may increase the frequency and/or severity of tonic-clonic seizures, requiring an increase in the dosage of standard anticonvulsant medication. In such cases, abrupt withdrawal of chronic diazepam may also be associated with a temporary increase in the frequency and/or severity of seizures.

10 OVERDOSAGE

Overdosage of benzodiazepines is characterized by central nervous system depression ranging from drowsiness to coma. In mild to moderate cases, symptoms can include drowsiness, confusion, dysarthria, lethargy, hypnotic state, diminished reflexes, ataxia, and hypotonia. Rarely, paradoxical or disinhibitory reactions (including agitation, irritability, impulsivity, violent behavior, confusion, restlessness, excitement, and talkativeness) may occur. In severe overdosage cases, patients may develop respiratory depression and coma. Overdosage of benzodiazepines in combination with other CNS depressants (including alcohol and opioids) may be fatal [see Warnings and Precautions (5.2)]. Markedly abnormal (lowered or elevated) blood pressure, heart rate, or respiratory rate raise the concern that additional drugs and/or alcohol are involved in the overdosage.

In managing benzodiazepine overdosage, employ general supportive measures, including intravenous fluids and airway maintenance. Flumazenil, a specific benzodiazepine receptor antagonist indicated for the complete or partial reversal of the sedative effects of benzodiazepines in the management of benzodiazepine overdosage, can lead to withdrawal and adverse reactions, including seizures, particularly in the context of mixed overdosage with drugs that increase seizure risk (e.g., tricyclic and tetracyclic antidepressants) and in patients with long-term benzodiazepine use and physical dependency. The risk of withdrawal seizures with flumazenil use may be increased in patients with epilepsy. Flumazenil is contraindicated in patients who have received a benzodiazepine for control of a potentially life-threatening condition (e.g., status epilepticus). If the decision is made to use flumazenil, it should be used as an adjunct to, not as a substitute for, supportive management of benzodiazepine overdosage. See the flumazenil injection Prescribing Information.

Consider contacting the Poison Help line (1-800-222-1222) or a medical toxicologist for additional overdosage management recommendations.

11 DESCRIPTION

Diazepam, the active ingredient of LIBERVANT, is a benzodiazepine anticonvulsant with the chemical name 7-chloro-1,3-dihydro-1-methyl-5-phenyl-2H-1,4-benzodiazepin-2-one; its empirical formula is C16H13ClN2O and its molecular weight is 284.7 g/mol. It is an odorless, white to practically white crystalline powder with a pKa of 3.4 and a partition coefficient of 2.9. It is practically insoluble in water and soluble in 96% ethanol, chloroform, and alcohol. The melting range for diazepam is 131°C to 135°C.The structural formula is as follows:

LIBERVANT is a buccal film that contains the active ingredient diazepam. Each film strip contains 5, 7.5, 10, 12.5, or 15mg of diazepam and the following inactive ingredients: benzyl alcohol, clove oil, EDTA disodium salt, FD&C Green #3, glycerol monooleate, hypromellose, peppermint oil, polyethylene oxide, polyvinylpyrrolidone, sodium phosphate, sucralose, vanillin, xanthan gum, water, and white ink.

12 CLINICAL PHARMACOLOGY

12.1 Mechanism of Action

The exact mechanism of action for diazepam is not fully understood, but is thought to involve potentiation of GABAergic neurotransmission resulting from binding at the benzodiazepine site of the GABAA receptor.

12.2 Pharmacodynamics

The effects of diazepam on the CNS are dependent on the dose administered, the route of administration, and the presence or absence of other medications.

12.3 Pharmacokinetics

The pharmacokinetics of diazepam and desmethyldiazepam following administration of LIBERVANT were investigated in adult healthy subjects and in pediatric and adult patients with epilepsy. The pharmacokinetics of diazepam were linear and dose-proportional in the recommended dose range [see Dosage and Administration (2.2)]. In pediatric patients 2 to 5 years of age, median maximum plasma concentration (Cmax) and median area under the plasma concentration curve for 4 hours after dosing (AUC0-4) of diazepam are approximately 2- to 3-times greater than in adults. The higher Cmax and higher AUC0-4 in pediatric patients 2 to 5 years of age are expected to provide adequate therapeutic exposures under both fed and fasted states.

Absorption

Following single doses of LIBERVANT administered to healthy adults under fasting conditions, diazepam peak concentration (Cmax) was reached in approximately 1 hour.

In pharmacokinetic studies of patients with epilepsy, pharmacokinetic parameters were similar between seizure state and non-seizure state.

Effect of Food

The pharmacokinetics of LIBERVANT were characterized under fasting, moderate fat, and high fat fed conditions in three clinical studies in adults. Under fed conditions a 33%-47% decrease in Cmax, but no significant change in AUC, was observed relative to fasting state. The recommended dosage of LIBERVANT [see Dosage and Administration (2.3)] considers the impact of food on pharmacokinetics of diazepam. As such, LIBERVANT may be administered without regard to food.

Distribution

The volume of distribution of diazepam was calculated to be approximately 1.46 L/kg. Both diazepam and its major active metabolite, desmethyldiazepam, bind extensively to plasma proteins (95%-98%).

Elimination

Metabolism

It has been reported in the literature that diazepam is extensively metabolized to one major active metabolite (desmethyldiazepam) and two minor active metabolites, 3-hydroxydiazepam (temazepam) and 3-hydroxy-N-diazepam (oxazepam) in plasma. At therapeutic doses, desmethyldiazepam is found in plasma at concentrations equivalent to those of diazepam while oxazepam and temazepam are not usually detectable. The metabolism of diazepam is primarily hepatic and involves demethylation (involving primarily CYP2C19 and CYP3A4) and 3-hydroxylation (involving primarily CYP3A4), followed by glucuronidation. The marked inter-individual variability in the clearance of diazepam reported in the literature is probably attributable to variability of CYP2C19 (which is known to exhibit genetic polymorphism; about 3-5% of Caucasians have little or no activity and are “poor metabolizers”) and CYP3A4. No inhibition was demonstrated in the presence of inhibitors selective for CYP2A6, CYP2C9, CYP2D6, CYP2E1, or CYP1A2, indicating that these enzymes are not significantly involved in metabolism of diazepam.

Excretion

The mean elimination half-lives of diazepam and desmethyldiazepam were found to be approximately 86 hours and 147 hours, respectively.

Specific Populations

Pediatric Patients

Literature reviews indicate that following IV administration (0.33 mg/kg), the half-life of diazepam in pediatric patients 2 to 5 years of age is approximately 15 to 21 hours.

Patients with Renal Impairment

The pharmacokinetics of diazepam have not been studied in subjects with renal impairment.

Patients with Hepatic Impairment

No pharmacokinetic studies were conducted with LIBERVANT in subjects with hepatic impairment. Literature review indicates that following administration of 0.1 to 0.15 mg/kg of diazepam intravenously, the half-life of diazepam was prolonged by two to five-fold in subjects with alcoholic cirrhosis (n=24) compared to age-matched control subjects (n=37) with a corresponding decrease in clearance by half. However, the exact degree of hepatic impairment in these subjects was not characterized in this literature.

Effect of Gender, Race, and Cigarette Smoking

No targeted pharmacokinetic studies have been conducted to evaluate the effect of gender, race, and cigarette smoking on the pharmacokinetics of diazepam. However, covariate analysis of a population of treated patients following administration of diazepam rectal gel, indicated that neither gender nor cigarette smoking had any effect on the pharmacokinetics of diazepam.

13 NONCLINICAL TOXICOLOGY

13.1 Carcinogenesis, Mutagenesis, Impairment of Fertility

Carcinogenesis

In studies in which mice and rats were administered diazepam in the diet at a dose of 75 mg/kg/day (approximately 10 and 20 times, respectively, a human dose of 0.6 mg/kg/day on a mg/m^2 basis) for 80 and 104 weeks, respectively, an increased incidence of liver tumors was observed in males of both species.

Mutagenesis

The data currently available are inadequate to determine the mutagenic potential of diazepam.

Impairment of Fertility

Reproduction studies of diazepam in rats showed decreases in the number of pregnancies and in the number of surviving offspring following administration of an oral dose of 100 mg/kg/day (approximately 27 times a human dose of 0.6 mg/kg/day on a mg/m^2 basis) prior to and during mating and throughout gestation and lactation. No adverse effects on fertility or offspring viability were noted at a dose of 80 mg/kg/day (approximately 22 times a human dose of 0.6 mg/kg/day on a mg/m^2 basis).

14 CLINICAL STUDIES

Safety and effectiveness of LIBERVANT in pediatric patients 2 to 5 years of age are supported by evidence from adequate and well-controlled studies of diazepam rectal gel in adult and pediatric patients, adult bioavailability studies comparing LIBERVANT with diazepam rectal gel, adult and pediatric LIBERVANT pharmacokinetic data, and an open-label safety study of LIBERVANT including patients 2 years to 5 years of age [see Clinical Pharmacology (12.3)].

The effectiveness of diazepam rectal gel has been established in two adequate and well-controlled clinical studies in pediatric patients 2 years of age and older and adults exhibiting intermittent, stereotypic episodes of frequent seizure activity (i.e., seizure clusters, acute repetitive seizures) that are distinct from a patient’s usual seizure pattern.

A randomized, double-blind study compared sequential doses of diazepam rectal gel and placebo in 91 patients (47 pediatric patients 2 years of age and older, 44 adults) exhibiting the appropriate seizure profile. The first dose was given at the onset of an identified episode. Pediatric patients 2 years of age and older were dosed again 4 hours after the first dose and were observed for a total of 12 hours. Adults were dosed at 4 and 12 hours after the first dose and were observed for a total of 24 hours. Primary outcomes for this study were seizure frequency during the period of observation and a global assessment that took into account the severity and nature of the seizures as well as their frequency.

The median seizure frequency for the diazepam rectal gel treated group was zero seizures per hour, compared to a median seizure frequency of 0.3 seizures per hour for the placebo group, a difference that was statistically significant (p <0.0001). All three categories of the global assessment (seizure frequency, seizure severity, and “overall”) were also found to be statistically significant in favor of diazepam rectal gel (p < 0.0001). The following histogram displays the results for the “overall” category of the global assessment.

Figure 1: Caregiver Overall Global Assessment of the Efficacy of Diazepam Rectal Gel

Patients treated with diazepam rectal gel experienced prolonged time-to-next-seizure compared to placebo (p = 0.0002) as shown in the following graph.

Figure 2: Kaplan-Meier Survival Analysis of Time-to-Next-Seizure - First Study

In addition, 62% of patients treated with diazepam rectal gel were seizure-free during the observation period compared to 20% of placebo patients.

Analysis of response by gender and age revealed no substantial differences between treatment in either of these subgroups. Analysis of response by race was considered unreliable, due to the small percentage of non-Caucasians.

A second double-blind study compared single doses of diazepam rectal gel and placebo in 114 patients (53 pediatric patients 2 years of age and older, 61 adults). The dose was given at the onset of the identified episode and patients were observed for a total of 12 hours. The primary outcome in this study was seizure frequency. The median seizure frequency for the diazepam rectal gel-treated group was 0 seizures per 12 hours, compared to a median seizure frequency of 2.0 seizures per 12 hours for the placebo group, a difference that was statistically significant (p < 0.03). Patients treated with diazepam rectal gel experienced prolonged time-to-next-seizure compared to placebo (p = 0.0072) as shown in Figure 3.

Figure 3: Kaplan-Meier Survival Analysis of Time-to-Next-Seizure - Second Study

In addition, 55% of patients treated with diazepam rectal gel were seizure-free during the observation period compared to 34% of patients receiving placebo. Overall, caregivers judged diazepam rectal gel to be more effective than placebo (p = 0.018), based on a 10 cm visual analog scale. In addition, investigators also evaluated the effectiveness of diazepam rectal gel and judged diazepam rectal gel to be more effective than placebo (p < 0.001).

An analysis of response by gender revealed a statistically significant difference between treatments in females but not in males in this study, and the difference between the 2 genders in response to the treatments reached borderline statistical significance. Analysis of response by race was considered unreliable, due to the small percentage of non-Caucasians.

16 HOW SUPPLIED/STORAGE AND HANDLING

16.1 How Supplied

LIBERVANT (diazepam buccal film) is supplied as five strengths of a rectangular green film imprinted in white ink according to their respective strengths and packaged in individual child-resistant polyester/foil laminated pouches (see Table 4).

Table 4: Available Packaging Configurations
Description | Contents | NDC
5 mg carton | 5 mg film strip imprinted with D5 | NDC 10094-305-01 (Individual pouch); NDC 10094-305-02 (Carton of 2 pouches)
7.5 mg carton | 7.5 mg film strip imprinted with D7●5 | NDC 10094-307-01 (Individual pouch); NDC 10094-307-02 (Carton of 2 pouches)
10 mg carton | 10 mg film strip imprinted with D10 | NDC 10094-310-01 (Individual pouch); NDC10094-310-02 (Carton of 2 pouches)
12.5 mg carton | 12.5 mg film strip imprinted with D12●5 | NDC 10094-312-01 (Individual pouch); NDC 10094-312-02 (Carton of 2 pouches)
15 mg carton | 15 mg film strip imprinted with D15 | NDC 10094-315-01 (Individual pouch); NDC 10094-315-02 (Carton of 2 pouches)

16.2 Storage and Handling

Store at 20°C to 25°C (68°F to 77°F); excursions permitted to 15°C to 30°C (59°F to 86°F) [see USP Controlled Room Temperature].

17 PATIENT COUNSELING INFORMATION

Advise the caregivers to read the FDA-approved patient labeling (Medication Guide and Instructions for Use).

Risks from Concomitant Use with Opioids

Inform caregivers that concomitant use of benzodiazepines, including LIBERVANT, and opioids may result in profound sedation, respiratory depression, coma, and death and not to use such drugs concomitantly unless supervised by a healthcare provider [see Warnings and Precautions (5.1), Drug Interactions (7.1)].

Abuse, Misuse, and Addiction

Inform caregivers that the use of LIBERVANT more frequently than recommended, even at recommended dosages, exposes users to risks of abuse, misuse, and addiction, which can lead to overdose and death, especially when used in combination with other medications (e.g., opioid analgesics), alcohol, and/or illicit substances. Inform caregivers about the signs and symptoms of benzodiazepine abuse, misuse, and addiction; to seek medical help if they develop these signs and/or symptoms; and on the proper disposal of unused drug [see Warnings and Precautions (5.2) and Drug Abuse and Dependence (9.2)].

Withdrawal Reactions

Inform caregivers that the use of LIBERVANT more frequently than recommended may lead to clinically significant physical dependence and that abrupt discontinuation or rapid dosage reduction of LIBERVANT may precipitate acute withdrawal reactions, which can be life-threatening. Inform caregivers that in some cases, patients taking benzodiazepines have developed a protracted withdrawal syndrome with withdrawal symptoms lasting weeks to more than 12 months [see Warnings and Precautions (5.3) and Drug Abuse and Dependence (9.2)].

Important Treatment Instructions

Instruct caregivers on what is and is not an intermittent and stereotypic episode of increased seizure activity (i.e., seizure cluster) that is appropriate for treatment, and the timing of administration in relation to the onset of the episode.

Instruct caregivers on what to observe following administration, and what would constitute an outcome requiring immediate medical attention.

Instruct caregivers not to administer a second dose of LIBERVANT if they are concerned by the patient’s breathing, the patient requires emergency rescue treatment with assisted breathing or intubation, or there is excessive sedation [see Use in Specific Populations (8.6)].

Advise caregivers on how frequently they can treat successive seizure cluster episodes over time.

CNS Depression
Advise caregivers to check with their healthcare provider before LIBERVANT is taken with other CNS depressants, such as other benzodiazepines, opioids, tricyclic antidepressants, sedating antihistamines, or alcohol [see Warnings and Precautions (5.4)].

If applicable, caution patients and caregivers about operating hazardous machinery, including driving a motor vehicle, or riding a bicycle, until they are reasonably certain that LIBERVANT does not affect them adversely (e.g., impair judgment, thinking or motor skills).

Suicidal Thinking and Behavior
Counsel patients, their caregivers, and their families that AEDs, including LIBERVANT, may increase the risk of suicidal thoughts and behavior and advise them of the need to be alert for the emergence or worsening of symptoms of depression, any unusual changes in mood or behavior, or the emergence of suicidal thoughts, behavior, or thoughts of self-harm. Caregivers should report behaviors of concern immediately to healthcare providers [see Warnings and Precautions (5.5)].

Proper Administration

Discuss the steps involved in the administration of LIBERVANT with the caregiver. The steps are described in the Medication Guide and Instruction for Use.

Manufactured by:
Aquestive Therapeutics
Warren, NJ

MEDICATION GUIDE
LIBERVANT™ (lih-ber-vant)
(diazepam)
buccal film, C-IV

What is the most important information I should know about LIBERVANT?

- LIBERVANT is a benzodiazepine medicine. Taking benzodiazepines with opioid medicines, alcohol, or other central nervous system (CNS) depressants (including street drugs) can cause severe drowsiness, breathing problems (respiratory depression), coma, and death. Get emergency help right away if any of the following happens:
  ◦ shallow or slowed breathing,
  ◦ breathing stops (which may lead to the heart stopping),
  ◦ excessive sleepiness (sedation).

Do not allow your child to drive a motor vehicle, operate heavy machinery, or ride a bicycle until you know how taking LIBERVANT with opioids affects your child.

- Risk of abuse, misuse, and addiction. LIBERVANT is used in children 2 to 5 years of age. The unapproved use of LIBERVANT has a risk for abuse, misuse, and addiction, which can lead to overdose and serious side effects including coma and death.
  ◦ Serious side effects including coma and death have happened in people who have abused or misused benzodiazepines, including diazepam (the active ingredient in LIBERVANT). These serious side effects may also includedelirium, paranoia, suicidal thoughts or actions, seizures, and difficulty breathing. Call your child’s healthcare provider or go to the nearest hospital emergency room right away if you get any of these serious side effects.
  ◦ Your child can develop an addiction even if your child takes LIBERVANT as prescribed by your child’s healthcare provider.
  ◦ Give LIBERVANT exactly as your child’s healthcare provider prescribed.
  ◦ Do not share LIBERVANT with other people.
  ◦ Keep LIBERVANT in a safe place and away from children.
- Physical dependence and withdrawal reactions. LIBERVANT is intended for use if needed in order to treat higher than usual seizure activity. Benzodiazepines, including LIBERVANT, can cause physical dependence and withdrawal reactions, especially if used daily. LIBERVANT is not intended for daily use.
  ◦ Do not suddenly stop giving LIBERVANT to your child without talking to your child’s healthcare provider. Stopping LIBERVANT suddenly can cause serious and life-threatening side effects, including, unusual movements, responses, or expressions, seizures that will not stop (status epilepticus), sudden and severe mental or nervous system changes, depression, seeing or hearing things that others do not see or hear, homicidal thoughts, an extreme increase in activity or talking, losing touch with reality, and suicidal thoughts or actions. Call your child’s healthcare provider or go to the nearest hospital emergency room right away if your child gets any of these symptoms.
  ◦ Some people who suddenly stop benzodiazepines have symptoms that can last for several weeks to more than 12 months including,anxiety, trouble remembering, learning, or concentrating, depression, problems sleeping, feeling like insects are crawling under your skin, weakness, shaking, muscle twitching, burning, or prickling feeling in your hands, arms, legs or feet, and ringing in your ears.
  ◦Physical dependence is not the same as drug addiction. Your child’s healthcare provider can tell you more about the differences between physical dependence and drug addiction.
  ◦ Do not give your child more LIBERVANT than prescribed or give LIBERVANT more often than prescribed.

- LIBERVANT can make your child sleepy or dizzy and can slow your child’s thinking and motor skills.
  ◦ Do not allow your child to drive a motor vehicle, operate machinery, or ride a bicycle until you know how LIBERVANT affects your child.
  ◦ Do not give other drugs that may make your child sleepy or dizzy while taking LIBERVANT without first talking to your child’s healthcare provider. When taken with drugs that cause sleepiness or dizziness, LIBERVANT may make your child’s sleepiness or dizziness much worse.

Like other antiepileptic medicines, LIBERVANT may cause suicidal thoughts or actions in a small number of people, about 1 in 500.
Call a healthcare provider right away if your child has any of these symptoms, especially if they are new, worse, or worry you:

- thoughts about suicide or dying

- attempts to commit suicide

- new or worse depression

- new or worse anxiety or irritability

- feeling agitated or restless

- an extreme increase in activity and talking (mania)

- trouble sleeping (insomnia)

- acting aggressive, being angry or violent

- new or worse panic attacks

- other unusual changes in behavior or mood

- acting on dangerous impulses

How can I watch for early symptoms of suicidal thoughts or actions?

- Pay attention to any changes, especially sudden changes in mood, behaviors, thoughts, or feelings.
- Keep all follow-up visits with your child’s healthcare provider as scheduled.

Call your child’s healthcare provider between visits as needed, especially if you are worried about symptoms. Suicidal thoughts or actions can be caused by things other than medicines. If your child has suicidal thoughts or actions, your child’s healthcare provider may check for other causes.

What is LIBERVANT?

- LIBERVANT is a prescription medicine used for the short-term treatment of seizure clusters (also known as “acute repetitive seizures”) that are different from a person’s usual seizure pattern in people 2 to 5 years of age.

LIBERVANT is a federally controlled substance (C-IV) because it contains diazepam that can be abused or lead to dependence. Keep LIBERVANT in a safe place to prevent misuse and abuse. Selling or giving away LIBERVANT may harm others and is against the law. It is not known if LIBERVANT is safe and effective in children less than 2 years of age and over 5 years of age.

Do not give LIBERVANT to your child if your child:

- is allergic to diazepam or any of the ingredients in LIBERVANT. See the end of this Medication Guide for a complete list of ingredients in LIBERVANT.
- has an eye problem called acute narrow angle glaucoma.

Before you give LIBERVANT, tell your child’s healthcare provider about all of your child’s medical conditions, including if your child:

- has a history of depression, mood problems, or suicidal thoughts or behavior.
- has liver or kidney problems.
- has asthma, emphysema, bronchitis, chronic obstructive pulmonary disease, or other breathing problems.

Tell your child’s healthcare provider about all the medicines your child takes, including prescription and over-the-counter medicines, vitamins, and herbal supplements. Taking LIBERVANT with certain other medicines can cause side effects or affect how well LIBERVANT or the other medicines work. Do not start or stop other medicines without talking to your child’s healthcare provider.

How should I give LIBERVANT?

- Read the Instructions for Use that comes with this Medication Guide for detailed information about the right way to give LIBERVANT.
- Give LIBERVANT exactly as your child’s healthcare provider tells you to.
- Do not change your child’s dosage unless your child’s healthcare provider tells you to change it.
- To give LIBERVANT:
  ◦ You as the caregiver must be able to tell the difference between cluster seizures and ordinary seizures.
  ◦ You as the caregiver must be comfortable in your ability to give LIBERVANT as instructed by your child’s healthcare provider and as instructed in the Instructions for Use at the end of this Medication Guide.
  ◦ You as the caregiver must understand your child’s healthcare provider’s instructions about when to use LIBERVANT.
- Your child’s healthcare provider will tell you:
  ◦ what seizure clusters are,
  ◦ exactly how much LIBERVANT to give to your child,
  ◦ when to give LIBERVANT,
  ◦ how to give LIBERVANT,
  ◦ what to do after you give LIBERVANT if the seizures do not stop or there is a change in breathing, behavior, or condition that worries you.
- Your child’s healthcare provider should show you how to give LIBERVANT the right way.
- You should carry LIBERVANT with you in case you need to give it to treat your child’s seizure clusters.
- Before a seizure cluster happens, family members, caregivers, and other people who may have to give LIBERVANT should know where you keep your LIBERVANT and how to give LIBERVANT.
- Each LIBERVANT comes in a sealed foil pouch. Do not open the foil pouch until you are ready to use it.
- Do not split LIBERVANT. The entire film should be placed on the inside of the cheek.
- Allow LIBERVANT to dissolve. Do not chew or swallow the film.
- Do not take with liquids.
- LIBERVANT can be taken with or without food.
- What should I do after LIBERVANT has been given:
  ◦ Note the time LIBERVANT was given and changes in the resting breathing rate.
  ◦ Your child’s healthcare provider may prescribe a second dose of LIBERVANT.
  ◦ If a second dose is needed, it may be given at least 4 hours after the first dose of LIBERVANT film is given.
  ◦ Do not give more than 2 doses of LIBERVANT to treat a seizure cluster.
  ◦ Do not give a second dose of LIBERVANT if:

▪ you are concerned about your child’s breathing,
▪ an emergency rescue treatment with breathing help is needed,
▪ or there is more sleepiness than normal.
Call for emergency medical help if any of the following happens:
◦ seizure behavior is different from other episodes the child has had.
◦ you are alarmed by how often the seizure happens, by how severe it is, by how long it lasts, or seizure is alarming.
◦ the child has unusual coloring or breathing.

- Do not use LIBERVANT for:
  ◦ more than 1 seizure cluster episode every 5 days and
  ◦ more than 5 episodes each month.
- Talk to your child’s healthcare provider about slowly stopping LIBERVANT to avoid withdrawal symptoms.
- If you give too much LIBERVANT, call your child’s healthcare provider or go to the nearest hospital emergency room right away.

What are the possible side effects of LIBERVANT?
LIBERVANT may cause serious side effects, including:

- See “What is the most important information I should know about LIBERVANT?”

The most common side effects of LIBERVANT are:

- sleepiness
- headache

These are not all the possible side effects of LIBERVANT.

Call your doctor for medical advice about side effects. You may report side effects to FDA at 1-800-FDA-1088.

How should I store LIBERVANT?

- Store LIBERVANT at room temperature between 68°F to 77°F (20°C to 25°C).
- Keep LIBERVANT in the foil pouch until ready to use.
- Keep LIBERVANT and all medicines out of the reach of children.

General information about the safe and effective use of LIBERVANT.
Medicines are sometimes prescribed for purposes other than those listed in a Medication Guide. Do not use LIBERVANT for a condition for which it was not prescribed. Do not give LIBERVANT to other people, even if they have the same symptoms that your child has. It may harm them.
You can ask your pharmacist or healthcare provider for information about LIBERVANT that is written for health professionals.

What are the ingredients in LIBERVANT?
Active ingredient: diazepam
Inactive ingredients: benzyl alcohol, clove oil, EDTA disodium salt, FD&C Green #3, glycerol monooleate, hypromellose, peppermint oil, polyethylene oxide, polyvinylpyrrolidone, sodium phosphate, sucralose, vanillin, xanthan gum, water, and white ink
Manufactured by: Aquestive Therapeutics, Warren NJ 07059, USA
For more information, go to www.aquestive.com or call 1-877-394-5045.

This Medication Guide is approved by the U.S. Food and Drug Administration Revision Date: 4/2024

INSTRUCTIONS FOR USE

LIBERVANT™ [lih-ber-vant]
(diazepam) buccal film

Family members, caregivers, and others who may need to administer LIBERVANT should read this Instructions for Use that comes with LIBERVANT before using it.

This Instructions for Use contains information on how to use LIBERVANT. This information does not take the place of talking to your child’s healthcare provider about your child’s medical condition or your child’s treatment. Ask your child’s healthcare provider or pharmacist if you or others who may need to administer LIBERVANT have any questions about how to use LIBERVANT the right way.

Important Information You Need to Know Before Using LIBERVANT

- For buccal use (place film on inside of cheek)
- Before using LIBERVANT, make sure your child’s healthcare provider shows you the right way to use it. If treatment is unable to be given and there is concern, call for emergency medical help right away.

Preparing to Use LIBERVANT

- Make sure hands are clean and dry before handling LIBERVANT so the film does not stick to your fingers.
- Check expiration date. Do not use if the expiration date has passed.

Using LIBERVANT

Step 1. Open Pouch and Remove Film from Pouch

- Fold foil pouch along solid line. While folded over, note where the vertical slit is and carefully tear down the side of the pouch at the slit along the arrow to open the pouch.
- Remove LIBERVANT film from foil pouch. Each foil pouch contains 1 dose of LIBERVANT.

Step 2. Place 1 Film on Inside of Cheek

- Do not give LIBERVANT film with liquids.
- Stretch either cheek open with one hand and place one film flat against the cheek with your other hand. Do not rub the film into the cheek with your finger.
- Place the film directly onto the inside of the cheek. Do not place film on teeth.
- Remove fingers from the cheek.
- If the film is spit out or blown out immediately, attempt to give another dose using a new film. If you cannot give the dose, call for emergency help.

Step 3. Allow Film to Dissolve

- If the film is accidentally swallowed or chewed, there is no need to give a replacement dose.
- LIBERVANT will stick to the inside of the cheek and begin to dissolve.
- The mouth can be closed or remain open while waiting.
- Saliva may be swallowed normally as the film dissolves.

What to do after LIBERVANT has been taken:

- Note the time LIBERVANT was taken and changes in the resting breath rate.
- Your child’s healthcare provider may prescribe a second dose of LIBERVANT. If a second dose is needed, it may be given at least 4 hours after the first dose of LIBERVANT film is given. Repeat Steps 1 through 3.
- Do not give a second dose if:
  ◦ you are concerned about your child’s breathing,
  ◦ an emergency rescue treatment with breathing help is needed,
  ◦ or there is more sleepiness than normal.
- Call for emergency medical help if any of the following occur:
  ◦ there is an increase in seizure frequency that does not stop after using LIBERVANT as instructed by your child’s healthcare provider
  ◦ seizure behavior is different from other episodes
  ◦ the frequency or severity of the seizure is alarming
  ◦ either skin color or breathing is alarming

Disposing of LIBERVANT

- Throw away (dispose of) empty foil pouch with the regular trash. Any films that were spit out or not used after opening should be flushed down the toilet or placed in the sink and rinsed with water until film is no longer visible.

For more information about LIBERVANT, go to www.aquestive.com or call 1-877-394-5045.

Manufactured by:
Aquestive Therapeutics
Warren, NJ 07059

This Instructions for Use has been approved by the U.S. Food and Drug Administration Issued Date: 4/2024

PACKAGE LABEL

PRINCIPAL DISPLAY PANEL

Rx Only
NDC 10094-305-01
Libervant
(diazepam) buccal film
5 mg
1 Buccal Film Dose

PACKAGE LABEL

PRINCIPAL DISPLAY PANEL

Rx Only
NDC 10094-305-02
Libervant
(diazepam) buccal film
5 mg
2 Pouches

PACKAGE LABEL

PRINCIPAL DISPLAY PANEL

Rx Only
NDC 10094-307-01
Libervant
(diazepam) buccal film
7.5 mg
1 Buccal Film Dose

PACKAGE LABEL

PRINCIPAL DISPLAY PANEL

Rx Only
NDC 10094-307-02
Libervant
(diazepam) buccal film
7.5 mg
2 Pouches

PACKAGE LABEL

PRINCIPAL DISPLAY PANEL

Rx Only
NDC 10094-310-01
Libervant
(diazepam) buccal film
10 mg
1 Buccal Film Dose

PACKAGE LABEL

PRINCIPAL DISPLAY PANEL

Rx Only
NDC 10094-310-02
Libervant
(diazepam) buccal film
10 mg
2 Pouches

PACKAGE LABEL

PRINCIPAL DISPLAY PANEL

Rx Only
NDC 10094-312-01
Libervant
(diazepam) buccal film
12.5 mg
1 Buccal Film Dose

PACKAGE LABEL

PRINCIPAL DISPLAY PANEL

Rx Only
NDC 10094-312-02
Libervant
(diazepam) buccal film
12.5 mg
2 Pouches

PACKAGE LABEL

PRINCIPAL DISPLAY PANEL

Rx Only
NDC 10094-315-01
Libervant
(diazepam) buccal film
15 mg
1 Buccal Film Dose

PACKAGE LABEL

PRINCIPAL DISPLAY PANEL

Rx Only
NDC 10094-315-02
Libervant
(diazepam) buccal film
15 mg
2 Pouches